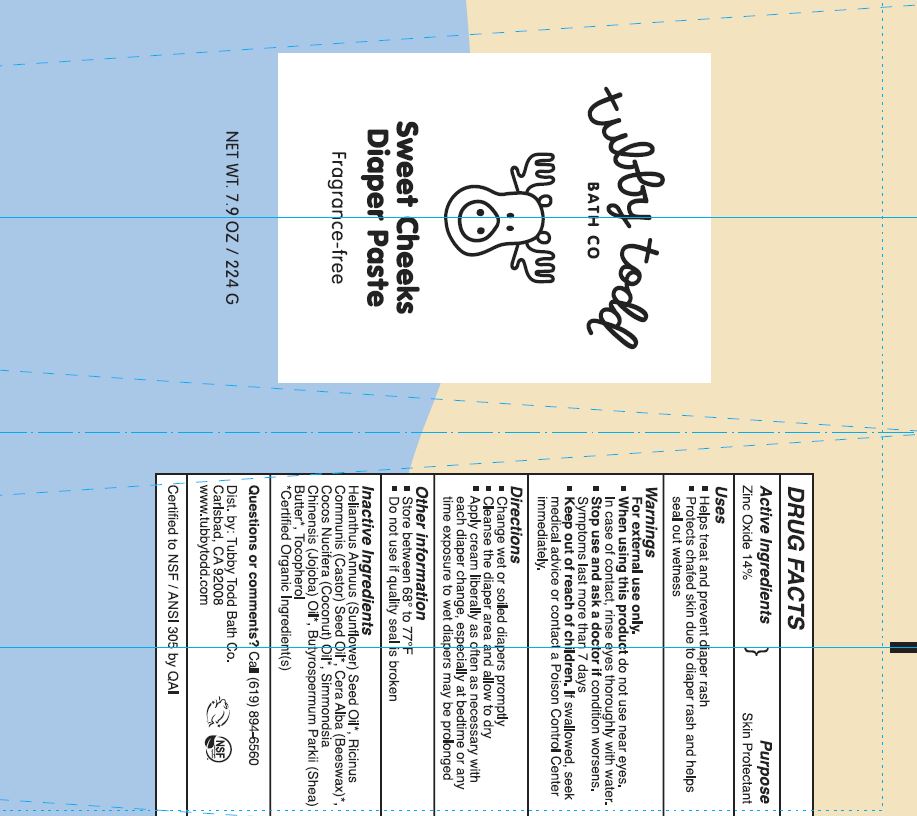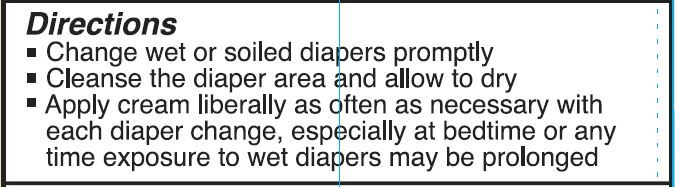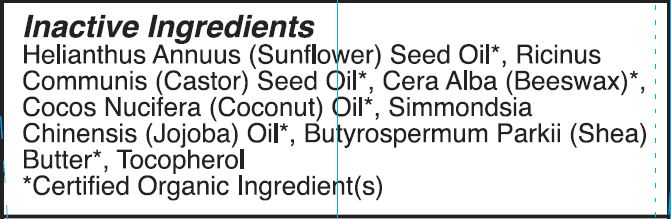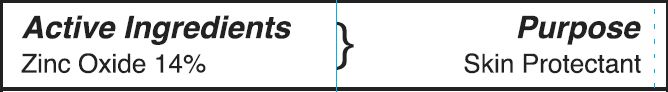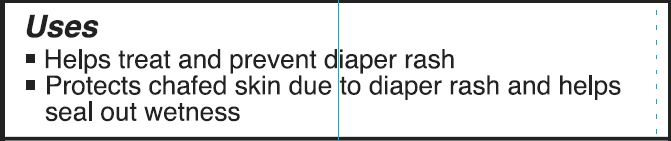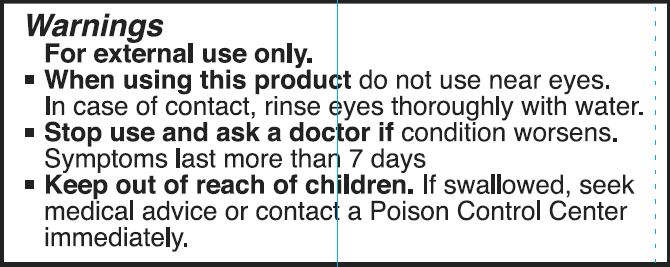 DRUG LABEL: Sweet Cheek Diaper Cream
NDC: 62932-260 | Form: OINTMENT
Manufacturer: Private Label Select Ltd CO
Category: otc | Type: HUMAN OTC DRUG LABEL
Date: 20211230

ACTIVE INGREDIENTS: ZINC OXIDE 14 g/100 g
INACTIVE INGREDIENTS: .DELTA.-TOCOPHEROL; COCONUT OIL; JOJOBA OIL; SHEA BUTTER; .ALPHA.-TOCOPHEROL, D-; .GAMMA.-TOCOPHEROL; .BETA.-TOCOPHEROL; WHITE WAX; SUNFLOWER OIL; CASTOR OIL

Tubby Todd Bath Co, Sweet Cheek Diaper Paste